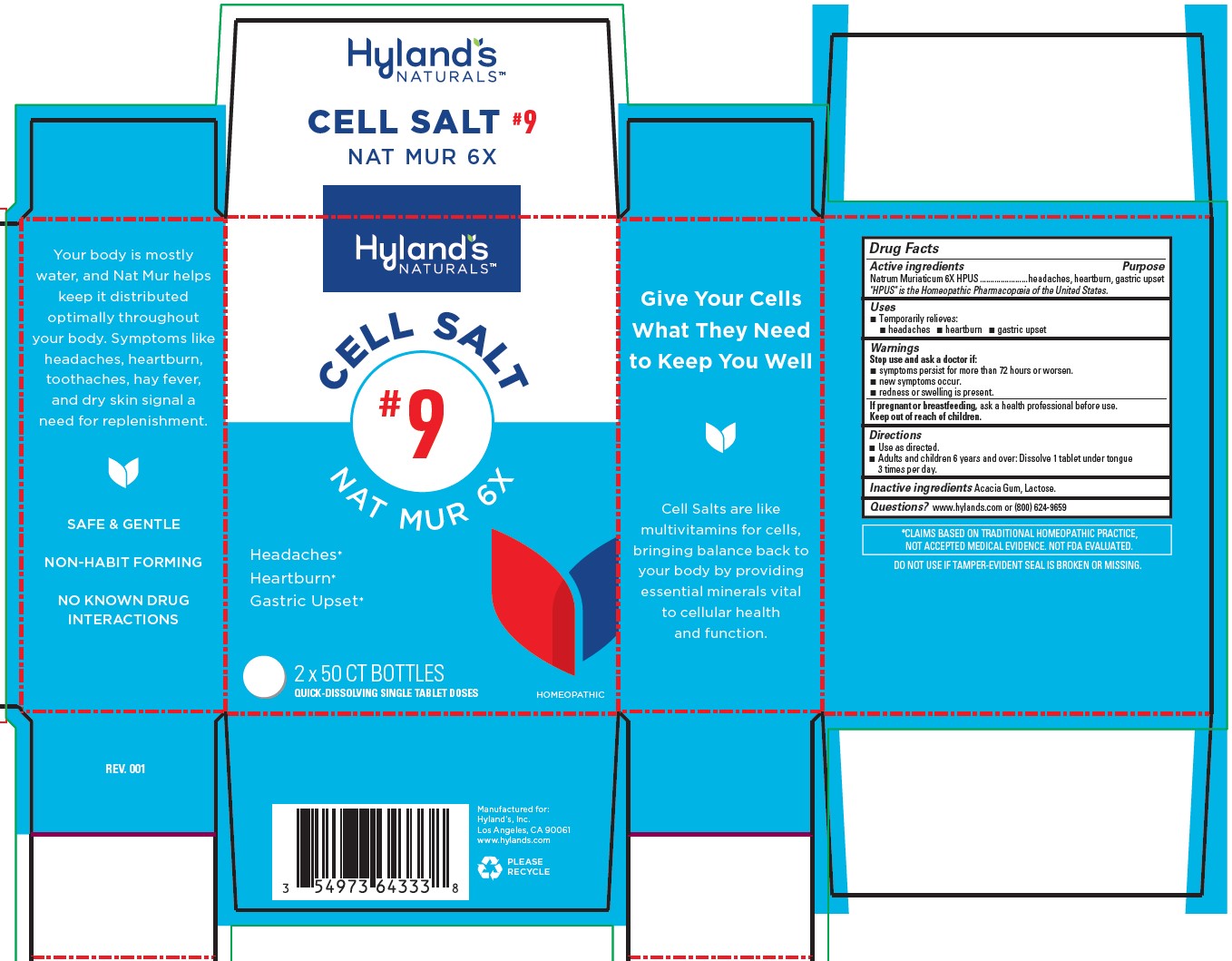 DRUG LABEL: Nat Mur
NDC: 54973-4080 | Form: TABLET
Manufacturer: Hyland's Inc.
Category: homeopathic | Type: HUMAN OTC DRUG LABEL
Date: 20221213

ACTIVE INGREDIENTS: SODIUM CHLORIDE 6 [hp_X]/1 1
INACTIVE INGREDIENTS: LACTOSE MONOHYDRATE; ACACIA

Cell Salt #9 Nat Mur 6X

PURPOSE

Temporarily relieves headaches, heartburn, gastric upset

Drug Facts

Active ingredients

Active ingredients | Purpose
Natrum Muriaticum 6X HPUS | headaches, heartburn, gastric upset

"HPUS" is the Homeopathic Pharmacopoeia of the United States.

Uses

■ Temporarily relieves:
■ headaches ■ heartburn ■ gastric upset

Warnings

Stop use and ask a doctor if

■symptoms persist for more than 72 hours or worsen.
■ new symptoms occur.
■ redness or swelling is present.

If pregnant or breastfeeding

ask a health professional before use.

Directions

■Use as directed.
■ Adults and children 6 years and over: Dissolve 1 tablet under tongue 3 times per day.

Inactive ingredients

Acacia Gum, Lactose.

Questions?

www.hylands.com or (800) 624-9659

PACKAGE LABEL - 2 x 50 TABLET BOTTLE CARTON

Hyland's

NATURALS™

CELL SALT

#9

NAT MUR 6X

Headaches*

Heartburn*

Gastric Upset*

2 x 50 CT BOTTLES

QUICK-DISSOLVING SINGLE TABLET DOSES

HOMEOPATHIC